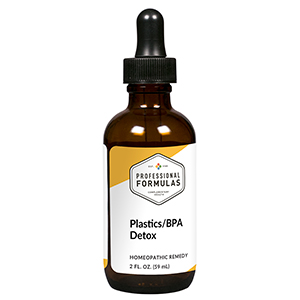 DRUG LABEL: Plastics/BPA Detox
NDC: 63083-6044 | Form: LIQUID
Manufacturer: Professional Complementary Health Formulas
Category: homeopathic | Type: HUMAN OTC DRUG LABEL
Date: 20190815

ACTIVE INGREDIENTS: ARCTIUM LAPPA ROOT OIL 3 [hp_X]/59 mL; TARAXACUM OFFICINALE 3 [hp_X]/59 mL; TRIFOLIUM PRATENSE FLOWER 3 [hp_X]/59 mL; BOS TAURUS BRAIN 6 [hp_X]/59 mL; BEEF KIDNEY 6 [hp_X]/59 mL; BEEF LIVER 6 [hp_X]/59 mL; BOS TAURUS LYMPH VESSEL 6 [hp_X]/59 mL; BISPHENOL A 12 [hp_X]/59 mL; METHYL METHACRYLATE 12 [hp_X]/59 mL; CARBONATE ION 12 [hp_X]/59 mL; SODIUM POLYSTYRENE SULFONATE 12 [hp_X]/59 mL; TRIS(2-ETHYLHEXYL)PHOSPHATE 12 [hp_X]/59 mL
INACTIVE INGREDIENTS: ALCOHOL; WATER

X44

ACTIVE INGREDIENTS

Arctium lappa 3X
Taraxacum officinale 3X
Trifolium pratense 3X
Brain 6X
Kidney 6X
Liver 6X
Lymph 6X
Bisphenol A (BPA) 12X, 30X, 60X
Methyl methacrylate 12X, 30X, 60X
Polycarbonate 12X, 30X, 60X
Polystyrene 12X, 30X, 60X
Polyvinyl chloride (PVC) 12X, 30X, 60X

QUESTIONS

Professional Formulas

PO Box 2034 Lake Oswego, OR 97035

INDICATIONS

For the temporary relief of itchy, dry, or irritated skin, runny nose, difficulty breathing, wheezing, or cough due to sensitivity to or exposure to plastics.*

PURPOSE

*Claims based on traditional homeopathic practice, not accepted medical evidence. Not FDA evaluated.

WARNINGS

In case of overdose, get medical help or contact a poison control center right away.

Keep out of the reach of children.

PREGNANCY OR BREAST FEEDING

If pregnant or breastfeeding, ask a healthcare professional before use.

DIRECTIONS

Place drops under tongue 30 minutes before/after meals. Adults and children 12 years and over: Take 10 drops up to 3 times per day. Consult a physician for use in children under 12 years of age.

OTHER INFORMATION

Tamper resistant. If seal is broken, do not use. After opening, close container tightly and store at room temperature away from heat.

INACTIVE INGREDIENTS

20% ethanol, purified water.

LABEL

Est 1985

Professional Formulas

Complementary Health

Plastics/BPA Detox

Homeopathic Remedy

2 FL. OZ. (59 mL)